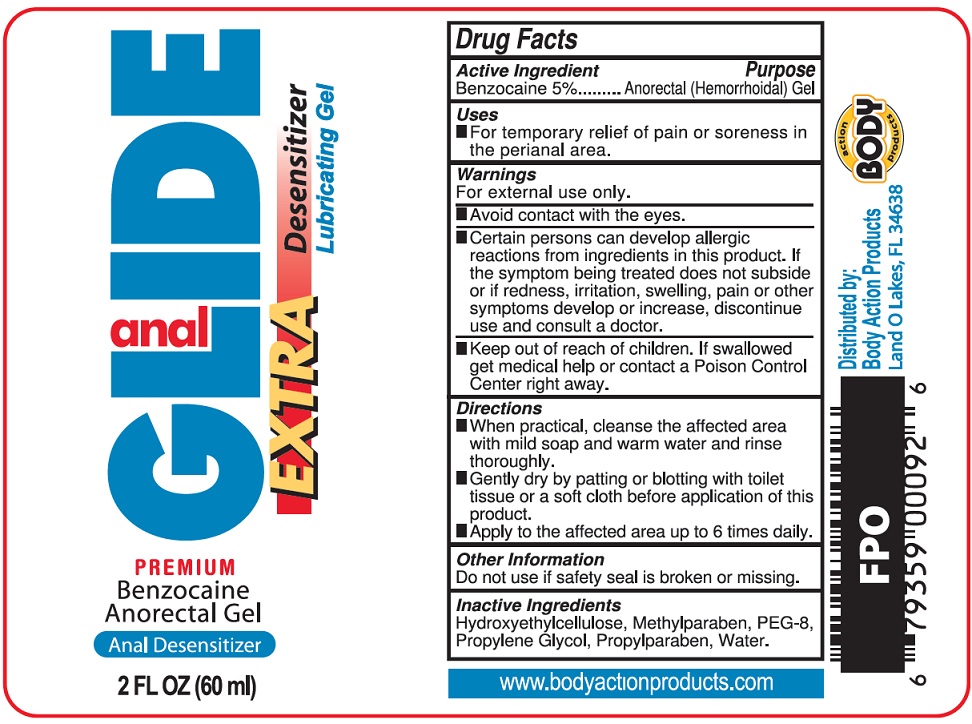 DRUG LABEL: BODY ACTION PRODUCTS Anal Glide Extra
NDC: 70742-287 | Form: GEL
Manufacturer: PRODUCT MAX GROUP INC
Category: otc | Type: HUMAN OTC DRUG LABEL
Date: 20250403

ACTIVE INGREDIENTS: BENZOCAINE 50 mg/1 mL
INACTIVE INGREDIENTS: HYDROXYETHYL CELLULOSE, UNSPECIFIED; METHYLPARABEN; POLYETHYLENE GLYCOL 400; PROPYLENE GLYCOL; PROPYLPARABEN; WATER

BODY ACTION PRODUCTS: Anal Glide Extra Gel

Active Ingredient

Benzocaine 5%

Purpose

Anorectal (Hemorrhoidal) Gel

Uses

- For temporary relief of pain or soreness in the perianal area.

Warnings

For external use only.

- Avoid contact with the eyes.
- Certain persons can develop allergic reactions from ingredients in this product. If the symptom being treated does not subside or if redness, irritation, swelling, pain or other symptoms develop or increase, discontinue use and consult a doctor.

Keep out of reach of children.

If swallowed get medical help or contact a Poison Control Center right away.

Directions

- When practial, cleanse the affected area with mild soap and warm water and rinse thoroughly.
- Gently dry by patting or blotting with toilet tissue or a soft cloth before application of this product.
- Apply to the affected area up to 6 times daily.

Other Information

Do not use if safety seal is broken or missing.

Inactive Ingredients

Hydroxyethylcellulose, Methylparaben, PEG-8, Propylene Glycol, Propylparaben, Water.